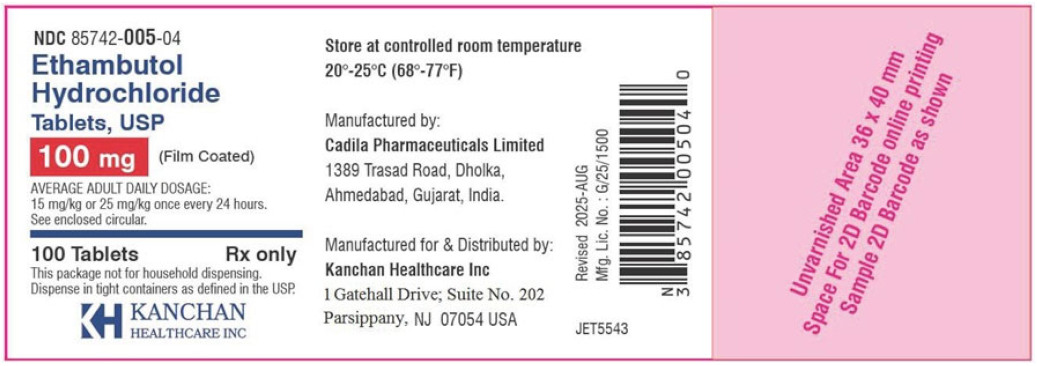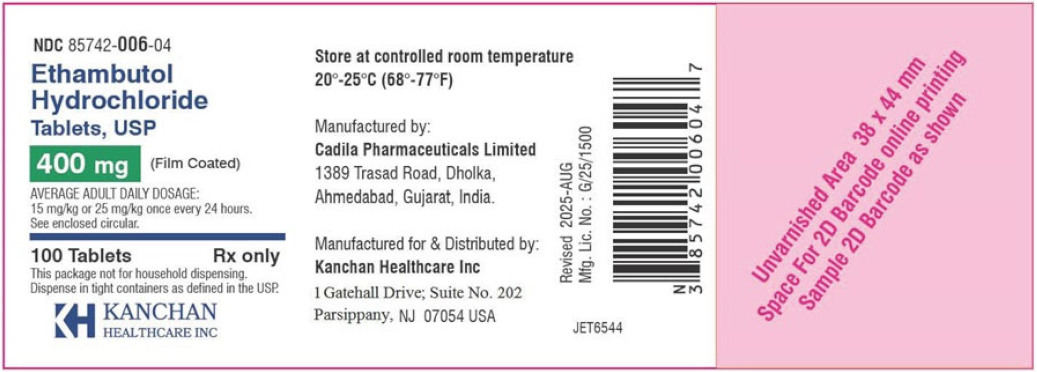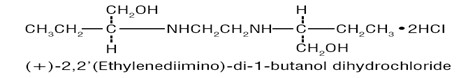 DRUG LABEL: Ethambutol Hydrochloride
NDC: 85742-006 | Form: TABLET, FILM COATED
Manufacturer: Kanchan Healthcare Inc
Category: prescription | Type: HUMAN PRESCRIPTION DRUG LABEL
Date: 20251121

ACTIVE INGREDIENTS: ETHAMBUTOL HYDROCHLORIDE 400 mg/1 1
INACTIVE INGREDIENTS: GELATIN; HYDROXYPROPYL CELLULOSE; MAGNESIUM STEARATE; SODIUM LAURYL SULFATE; SORBITOL; STEARIC ACID; SUCROSE; TITANIUM DIOXIDE

100 mg and 400 mg
Rx only

DESCRIPTION

ETHAMBUTOL HYDROCHLORIDE is an oral chemotherapeutic agent which is specifically effective against actively growing microorganisms of the genus Mycobacterium, including M. tuberculosis. The structural formula is:

ETHAMBUTOL HYDROCHLORIDE (HCL) 100 and 400 mg tablets contain the following inactive ingredients: Gelatin, Hydroxypropyl Methylcellulose, Magnesium Stearate, Sodium Lauryl Sulfate, Sorbitol, Stearic Acid, Sucrose, Titanium Dioxide and other ingredients.

CLINICAL PHARMACOLOGY

ETHAMBUTOL HCL, following a single oral dose of 25 mg/kg of body weight, attains a peak of 2 to 5 mcg/mL in serum 2 to 4 hours after administration. When the drug is administered daily for longer periods of time at this dose, serum levels are similar. The serum level of ETHAMBUTOL HCL falls to undetectable levels by 24 hours after the last dose except in some patients with abnormal renal function. The intracellular concentrations of erythrocytes reach peak values approximately twice those of plasma and maintain this ratio throughout the 24 hours.

During the 24-hour period following oral administration of ETHAMBUTOL HCl approximately 50 percent of the initial dose is excreted unchanged in the urine, while an additional 8 to 15 percent appears in the form of metabolites. The main path of metabolism appears to be an initial oxidation of the alcohol to an aldehydic intermediate, followed by conversion to a dicarboxylic acid. From 20 to 22 percent of the initial dose is excreted in the feces as unchanged drug. No drug accumulation has been observed with consecutive single daily doses of 25 mg/kg in patients with normal kidney function, although marked accumulation has been demonstrated in patients with renal insufficiency.

ETHAMBUTOL HCl diffuses into actively growing Mycobacterium cells such as tubercle bacilli. ETHAMBUTOL HCl appears to inhibit the synthesis of one or more metabolites, thus causing impairment of cell metabolism, arrest of multiplication, and cell death. No cross resistance with other available antimycobacterial agents has been demonstrated.

ETHAMBUTOL HCl has been shown to be effective against strains of Mycobacterium tuberculosis but does not seem to be active against fungi, viruses, or other bacteria. Mycobacterium tuberculosis strains previously unexposed to ETHAMBUTOL HCL have been uniformly sensitive to concentrations of 8 or less mcg/mL, depending on the nature of the culture media. When ETHAMBUTOL HCl has been used alone for treatment of tuberculosis, tubercle bacilli from these patients have developed resistance to ETHAMBUTOL HCl (ethambutol hydrochloride) by in vitro susceptibility tests; the development of resistance has been unpredictable and appears to occur in a step-like manner. No cross resistance between ETHAMBUTOL HCl and other antituberculous drugs has been reported. ETHAMBUTOL HCl has reduced the incidence of the emergence of mycobacterial resistance to isoniazid when both drugs have been used concurrently. An agar diffusion microbiologic assay, based upon inhibition of Mycobacterium smegmatis (ATCC 607) may be used to determine concentrations of ETHAMBUTOL HCl in serum and urine.

ANIMAL PHARMACOLOGY

Toxicological studies in dogs on high prolonged doses produced evidence of myocardial damage and failure, and depigmentation of the tapetum lucidum of the eyes, the significance of which is not known. Degenerative changes in the central nervous system, apparently not dose-related, have also been noted in dogs receiving ethambutol hydrochloride over a prolonged period. In the rhesus monkey, neurological signs appeared after treatment with high doses given daily over a period of several months. These were correlated with specific serum levels of ethambutol and with definite neuroanatomical changes in the central nervous system. Focal interstitial carditis was also noted in monkeys which received ethambutol hydrochloride in high doses for a prolonged period.

INDICATIONS

ETHAMBUTOL HCl is indicated for the treatment of pulmonary tuberculosis. It should not be used as the sole antituberculous drug, but should be used in conjunction with at least one other antituberculous drug. Selection of the companion drug should be based on clinical experience, considerations of comparative safety, and appropriate in vitro susceptibility studies. In patients who have not received previous antituberculous therapy, ie, initial treatment, the most frequently used regimens have been the following:

ETHAMBUTOL HCl plus isoniazid

ETHAMBUTOL HCl plus isoniazid plus streptomycin.

In patients who have received previous antituberculous therapy, mycobacterial resistance to other drugs used in initial therapy is frequent. Consequently, in such retreatment patients, ETHAMBUTOL HCl should be combined with at least one of the second line drugs not previously administered to the patient and to which bacterial susceptibility has been indicated by appropriate in vitro studies. Antituberculous drugs used with ETHAMBUTOL HCl have included cycloserine, ethionamide, pyrazinamide, viomycin and other drugs. Isoniazid, aminosalicylic acid, and streptomycin have also been used in multiple drug regimens. Alternating drug regimens have also been utilized.

CONTRAINDICATIONS

ETHAMBUTOL HCl is contraindicated in patients who are known to be hypersensitive to this drug. It is also contraindicated in patients with known optic neuritis unless clinical judgment determines that it may be used. ETHAMBUTOL HCl is contraindicated in patients who are unable to appreciate and report visual side effects or changes in vision (e.g., young children, unconscious patients).

WARNINGS

ETHAMBUTOL HCl may produce decreases in visual acuity which appear to be due to optic neuritis. This effect may be related to dose and duration of treatment. This effect is generally reversible when administration of the drug is discontinued promptly. However, irreversible blindness has been reported. (See PRECAUTIONS and ADVERSE REACTIONS).

Liver toxicities including fatalities have been reported (see ADVERSE REACTIONS). Baseline and periodic assessment of hepatic function should be performed.

PRECAUTIONS

ETHAMBUTOL HCl is not recommended for use in pediatric patients under thirteen years of age since safe conditions for use have not been established.

Patients with decreased renal function need the dosage reduced as determined by serum levels of ETHAMBUTOL HCl, since the main path of excretion of this drug is by the kidneys.

Because this drug may have adverse effects on vision, physical examination should include ophthalmoscopy, finger perimetry and testing of color discrimination. In patients with visual defects such as cataracts, recurrent inflammatory conditions of the eye, optic neuritis, and diabetic retinopathy, the evaluation of changes in visual acuity is more difficult, and care should be taken to be sure the variations in vision are not due to the underlying disease conditions. In such patients, consideration should be given to relationship between benefits expected and possible visual deterioration since evaluation of visual changes is difficult. (For recommended procedures, see next paragraphs under ADVERSE REACTIONS .)

As with any potent drug, baseline and periodic assessment of organ system functions, including renal, hepatic, and hematopoietic, should be performed.

Drug Interactions

The results of a study of coadministration of ETHAMBUTOL HCl (50mg/kg) with an aluminum hydroxide containing antacid to 13 patients with tuberculosis showed a reduction of mean serum concentrations and urinary excretion of ethambutol of approximately 20% and 13%, respectively, suggesting that the oral absorption of ethambutol may be reduced by these antacid products. It is recommended to avoid concurrent administration of ethambutol with aluminum hydroxide containing antacids for at least 4 hours following ethambutol administration.

Pregnancy

Teratogenic Effects: Pregnancy Category C.

There are no adequate and well-controlled studies in pregnant women. There are reports of ophthalmic abnormalities occurring in infants born to women on antituberculous therapy that included ETHAMBUTOL HCl. ETHAMBUTOL HCl should be used during pregnancy only if the benefit justifies the potential risk to the fetus.

ETHAMBUTOL HCl has been shown to be teratogenic in pregnant mice and rabbits when given in high doses. When pregnant mice or rabbits were treated with high doses of ethambutol hydrochloride, fetal mortality was slightly but not significantly (P>0.05) increased. Female rats treated with ethambutol hydrochloride displayed slight but insignificant (P>0.05) decreases in fertility and litter size. In fetuses born of mice treated with high doses of ETHAMBUTOL HCl during pregnancy, a low incidence of cleft palate, exencephaly and abnormality of the vertebral column were observed. Minor abnormalities of the cervical vertebra were seen in the newborn of rats treated with high doses of ethambutol hydrochloride during pregnancy. Rabbits receiving high doses of ETHAMBUTOL HCl during pregnancy gave birth to two fetuses with monophthalmia, one with a shortened right forearm accompanied by bilateral wrist-joint contracture and one with hare lip and cleft palate.

Nursing Mothers

ETHAMBUTOL HCl is excreted into breast milk. The use of ETHAMBUTOL HCl should be considered only if the expected benefit to the mother outweighs the potential risk to the infant.

Pediatric Use

ETHAMBUTOL HCl (ethambutol hydrochloride) is not recommended for use in pediatric patients under thirteen years of age since safe conditions for use have not been established.

Geriatric Use

There are limited data on the use of ETHAMBUTOL HCl in the elderly. One study of 101 patients, 65 years and older, on multiple drug antituberculosis regimens included 94 patients on ETHAMBUTOL HCl. No differences in safety or tolerability were observed in these patients compared with that reported in adults in general. Other reported clinical experience has not identified differences in responses between the elderly and younger patients, but greater sensitivity of some older individuals cannot be ruled out.

ADVERSE REACTIONS

ETHAMBUTOL HCl may produce decreases in visual acuity, including irreversible blindness, which appear to be due to optic neuritis. Optic neuropathy including optic neuritis or retrobulbar neuritis occurring in association with ethambutol therapy may be characterized by one or more of the following events: decreased visual acuity, scotoma, color blindness, and/or visual defect. These events have also been reported in the absence of a diagnosis of optic or retrobulbar neuritis.

Patients should be advised to report promptly to their physician any change of visual acuity.

The change in visual acuity may be unilateral or bilateral and hence each eye must be tested separately and both eyes tested together. Testing of visual acuity should be performed before beginning ETHAMBUTOL HCl therapy and periodically during drug administration, except that it should be done monthly when a patient is on a dosage of more than 15 mg per kilogram per day. Snellen eye charts are recommended for testing of visual acuity. Studies have shown that there are definite fluctuations of one or two lines of the Snellen chart in the visual acuity of many tuberculous patients not receiving ETHAMBUTOL HCl.

The following table may be useful in interpreting possible changes in visual acuity attributable to ETHAMBUTOL HCl.

Initial Snellen Reading | Reading Indicating Significant Decrease | Significant Number of Lines | Decreased Number of Points
20/13 | 20/25 | 3 | 12
20/15 | 20/25 | 2 | 10
20/20 | 20/30 | 2 | 10
20/25 | 20/40 | 2 | 15
20/30 | 20/50 | 2 | 20
20/40 | 20/70 | 2 | 30
20/50 | 20/70 | 1 | 20

In general, changes in visual acuity less than those indicated under “Significant Number of Lines” and “Decrease Number of Points” may be due to chance variation, limitations of the testing method, or physiologic variability. Conversely, changes in visual acuity equaling or exceeding those under “Significant Number of Lines” and “Decrease Number of Points” indicate need for retesting and careful evaluation of the patient's visual status. If careful evaluation confirms the magnitude of visual change and fails to reveal another cause, ETHAMBUTOL HCl should be discontinued and the patient reevaluated at frequent intervals. Progressive decreases in visual acuity during therapy must be considered to be due to ETHAMBUTOL HCl.

If corrective glasses are used prior to treatment, these must be worn during visual acuity testing. During 1 to 2 years of therapy, a refractive error may develop which must be corrected in order to obtain accurate test results. Testing the visual acuity through a pinhole eliminates refractive error. Patients developing visual abnormality during ETHAMBUTOL HCl treatment may show subjective visual symptoms before, or simultaneously with, the demonstration of decreases in visual acuity, and all patients receiving ETHAMBUTOL HCl should be questioned periodically about blurred vision and other subjective eye symptoms.

Recovery of visual acuity generally occurs over a period of weeks to months after the drug has been discontinued. Some patients have received ETHAMBUTOL HCl (ethambutol hydrochloride) again after such recovery without recurrence of loss of visual acuity. Other adverse reactions reported include: hypersensitivity, anaphylactic/anaphylactoid reaction, dermatitis, erythema multiforme, pruritus, and joint pain; anorexia, nausea, vomiting, gastrointestinal upset, and abdominal pain; fever, malaise, headache, and dizziness; mental confusion, disorientation, and possible hallucinations; thrombocytopenia, leukopenia, and neutropenia. Numbness and tingling of the extremities due to peripheral neuritis have been reported. Elevated serum uric acid levels occur and precipitation of acute gout has been reported. Pulmonary infiltrates, with or without eosinophilia, also have been reported during ETHAMBUTOL HCl therapy. Liver toxicities, including fatalities, have been reported. (See WARNINGS).

Since ETHAMBUTOL HCl is recommended for therapy in conjunction with one or more other antituberculous drugs, these changes may be related to the concurrent therapy. Hypersensitivity syndrome consisting of cutaneous reaction (such as rash or exfoliative dermatitis), eosinophilia, and one or more of the following: hepatitis, pneumonitis, nephritis, myocarditis, pericarditis. Fever and lymphadenopathy may be present.

DOSAGE and ADMINISTRATION

ETHAMBUTOL HCl should not be used alone, in initial treatment or in tretreatment. ETHAMBUTOL HCl should be administered on a once every 24-hour basis only.

Absorption is not significantly altered by administration with food. Therapy, in general, should be continued until bacteriological conversion has become permanent and maximal clinical improvement has occurred.

ETHAMBUTOL HCl is not recommended for use in pediatric patients under thirteen years of age since safe conditions for use have not been established.

Initial Treatment: In patients who have not received previous antituberculous therapy, administer ETHAMBUTOL HCl 15 mg/kg (7 mg/lb) of body weight, as a single oral dose once every 24 hours. In the more recent studies, isoniazid has been administered concurrently in a single, daily, oral dose.

Retreatment: In patients who have received previous antituberculous therapy, administer ETHAMBUTOL HCl 25 mg/kg (11 mg/lb) of body weight, as a single oral dose once every 24 hours. Concurrently administer at least one other antituberculous drug to which the organisms have been demonstrated to be susceptible by appropriate in vitro tests. Suitable drugs usually consist of those not previously used in the treatment of the patient. After 60 days of ETHAMBUTOL HCl administration, decrease the dose to 15 mg/kg (7mg/lb) of body weight, and administer as a single oral dose once every 24 hours.

During the period when a patient is on a daily dose of 25 mg/kg, monthly eye examinations are advised.

See Table for easy selection of proper weight-dose tablet(s).

Weight-Dose Table
15 mg/kg (7 mg/lb) Schedule
Weight Range Pounds | Dose Kilograms In mg
Under 85 lbs | Under 37 Kg……….500
85 – 94.5 | 37-43…………..600
95 – 109.5 | 43-50…………..700
110– 124.5 | 50-57…………..800
125– 139.5 | 57-64…………..900
140– 154.5 | 64-71…………..1000
155– 169.5 | 71-79…………..1100
170 – 184.5 | 79-84…………..1200
185– 199.5 | 84-90…………..1300
200– 214.5 | 90-97…………..1400
215 and Over | Over 97…………..1500
25 mg/kg (11 mg/lb) Schedule
Under 85 lbs. | Under 38 kg…………..900
85 – 92.5 | 38-42…………..1000
93 – 101.5 | 42-45.5…………..1100
102– 109.5 | 45.5-50…………..1200
110 – 118.5 | 50-54…………..1300
119 – 128.5 | 54-58…………..1400
129 – 136.5 | 58-62…………..1500
137 – 146.5 | 62-67…………..1600
147 – 155.5 | 67-71…………..1700
156 – 164.5 | 71-75…………..1800
165– 173.5 | 75-79…………..1900
174– 182.5 | 79-83…………..2000
183– 191.5 | 83-87…………..2100
192– 199.5 | 87-91…………..2200
200– 209.5 | 91-95…………..2300
210– 218.5 | 95-99…………..2400
219 and Over | Over 99…………2500

HOW SUPPLIED

Ethambutol hydrochloride Tablets USP

100 mg – round, convex, white, film coated tablets engraved E6 on one side are supplied as follows:
NDC 85742-005-04 - Bottle of 100

400 mg – round, convex, white, scored, film coated tablets engraved with E to the left and 7 to the right of the score on one side are supplied as follows:
NDC 85742-006-04 - Bottle of 100

Store at controlled room temperature 20° to 25° C (68° to 77° F).

To report SUSPECTED ADVERSE REACTIONS, contact Kanchan Healthcare Inc at (833) 845-2624 or kanchan_micc@mitconbiopharma.com or FDA at 1-800-FDA-1088 or www.fda.gov/medwatch

Manufactured by :
Cadila Pharmaceuticals Limited
1389 Trasad Road,
Dholka, Ahmedabad,
Gujarat, India.

Manufactured for & Distributed by:
Kanchan Healthcare Inc.
1 Gatehall Drive: Suite No. 202
Parsippany, NJ 07054 USA

Revised 08/2025

Principal Display Panel - Ethambutol 100mg

NDC 85742-005-04

Ethambutol
Hydrochloride
Tablets, USP
100mg (Film Coated)
AVERAGE ADULT DAILY DOSAGE:
15 mg/kg or 25 mg/kg once every 24 hours.
See enclosed circular.
100 Tablets Rx only
This package not for household dispensing.
Dispense in tight containers as defined in the USP.
KANCHAN
HEALTHCARE INC

Principal Display Panel - Ethambutol 400mg

NDC 85742-006-04

Ethambutol
Hydrochloride
Tablets, USP
400mg (Film Coated)
AVERAGE ADULT DAILY DOSAGE:
15 mg/kg or 25 mg/kg once every 24 hours.
See enclosed circular.
100 Tablets Rx only
This package not for household dispensing.
Dispense in tight containers as defined in the USP.
KANCHAN
HEALTHCARE INC